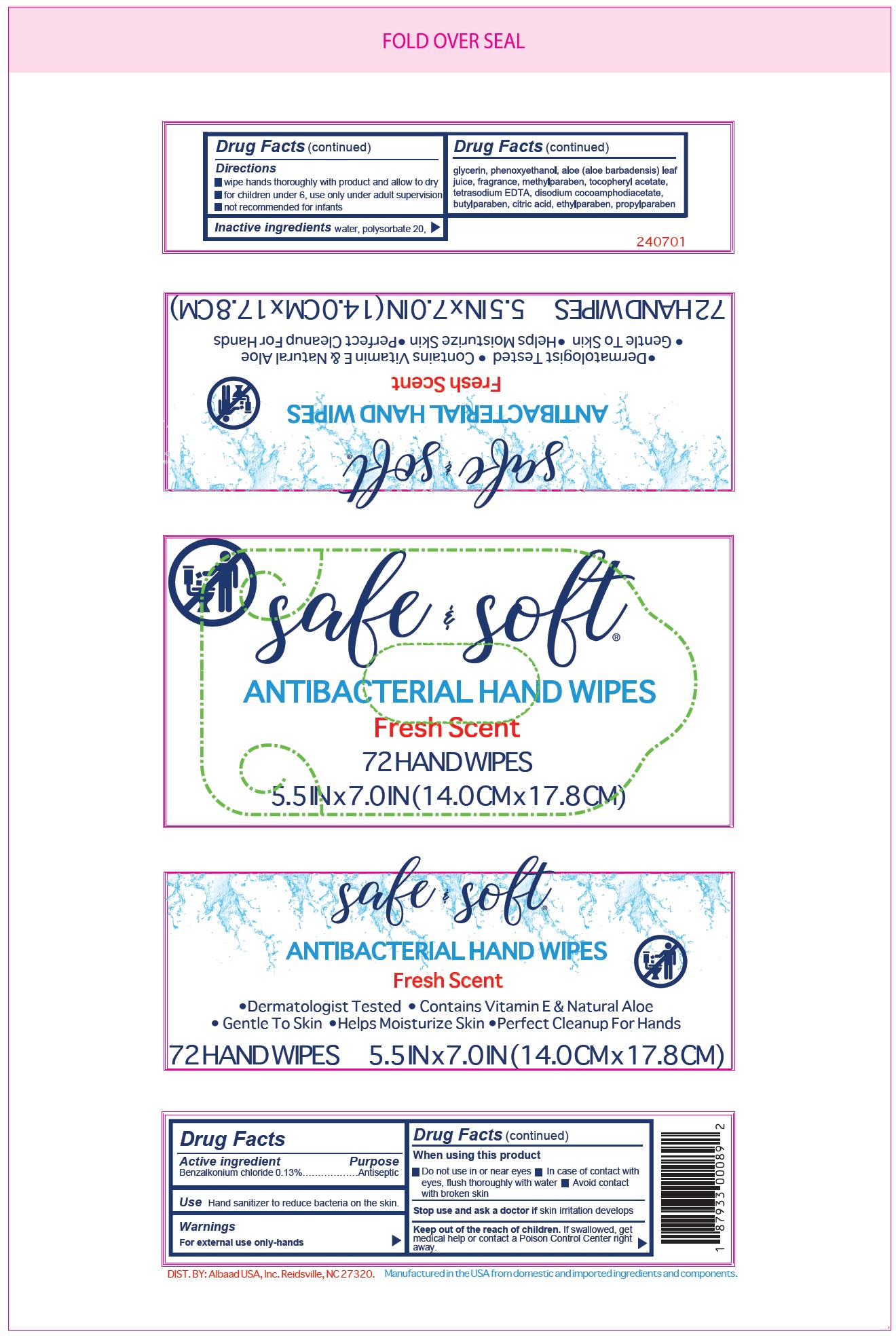 DRUG LABEL: Safe and Soft Antibacterial Hand Wipes
NDC: 23957-001 | Form: CLOTH
Manufacturer: Albaad USA, Inc
Category: otc | Type: HUMAN OTC DRUG LABEL
Date: 20220715

ACTIVE INGREDIENTS: BENZALKONIUM CHLORIDE 1.3 mg/1 g
INACTIVE INGREDIENTS: WATER; POLYSORBATE 20; GLYCERIN; PHENOXYETHANOL; ALOE VERA LEAF; METHYLPARABEN; .ALPHA.-TOCOPHEROL ACETATE; EDETATE SODIUM; DISODIUM COCOAMPHODIACETATE; BUTYLPARABEN; CITRIC ACID MONOHYDRATE; ETHYLPARABEN; PROPYLPARABEN

Safe and Soft Antibacterial Hand Wipes

Active ingredient

Benzalkonium chloride 0.13%

Purpose

Antiseptic

Use

Hand sanitizer to reduce bacteria on the skin.

Warnings

For external use only-hands

When using this product

- Do not use in or near eyes
- In case of contact with eyes, flush thoroughly with water
- Avoid contact with broken skin

Stop use and ask a doctor if

skin irritation develops

Keep out of the reach of children.

If swallowed, get medical help or contact a Poison Control Center right away.

Directions

- wipe hands thoroughly with product and allow to dry
- for children under 6, use only under adult supervision
- not recommended for infants

Inactive ingredients

water, polysorbate 20, glycerin, phenoxyethanol, aloe (aloe barbadensis) leaf juice, fragrance, methylparaben, tocopheryl acetate, tetrasodium EDTA, disodium cocoamphodiacetate, butylparaben, citric acid, ethylparaben, propylparaben